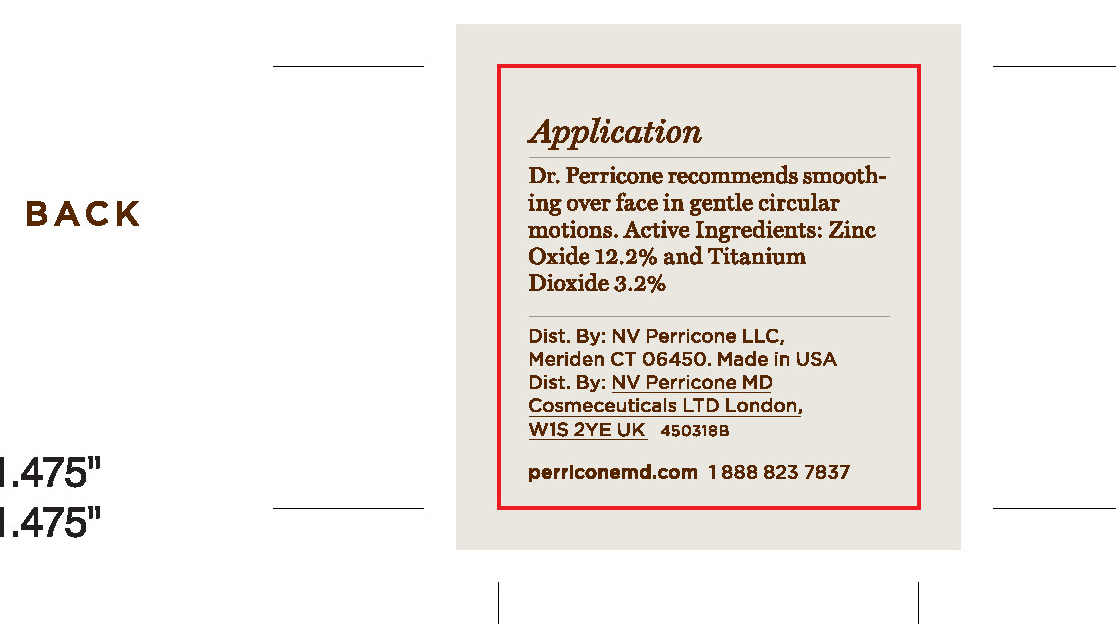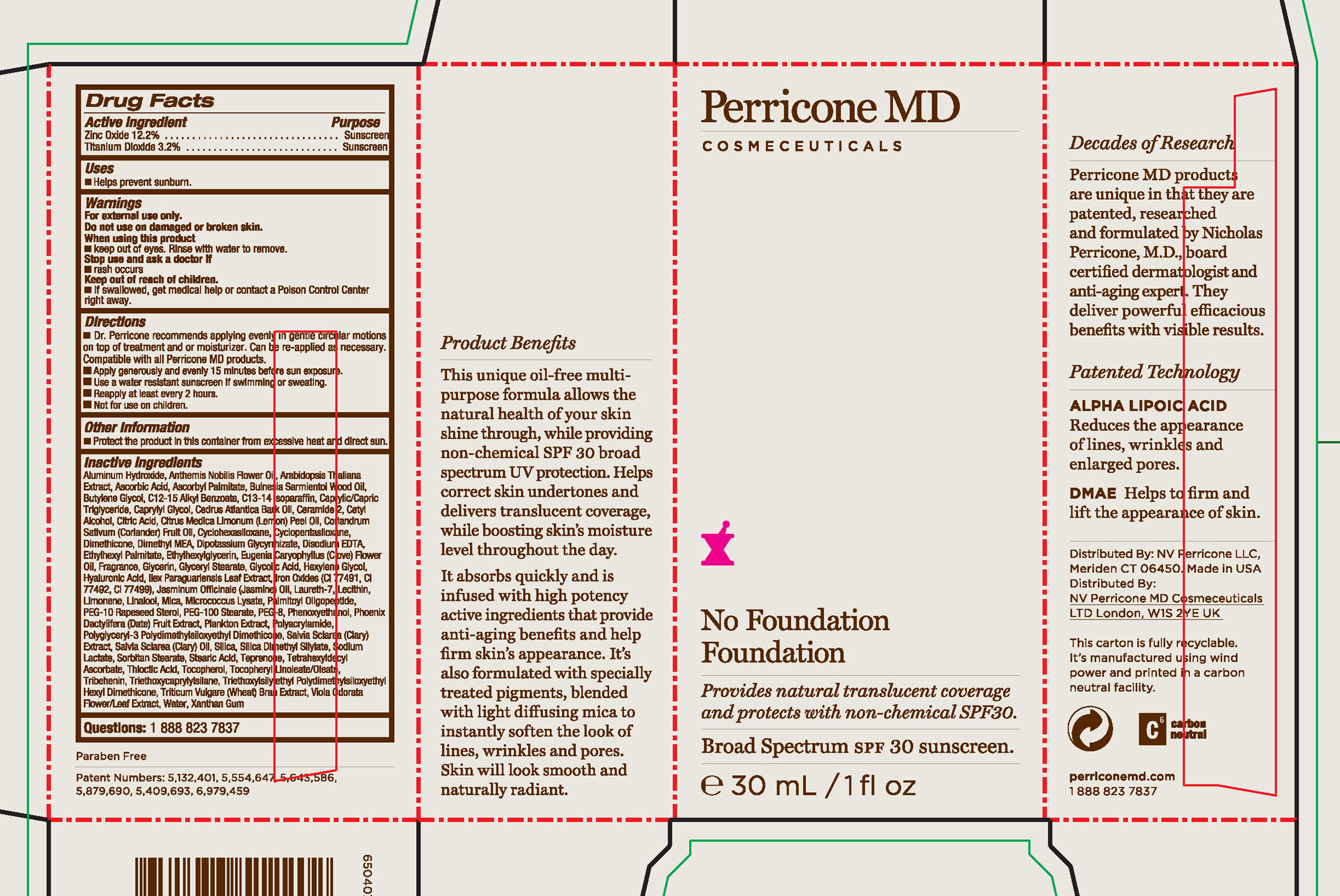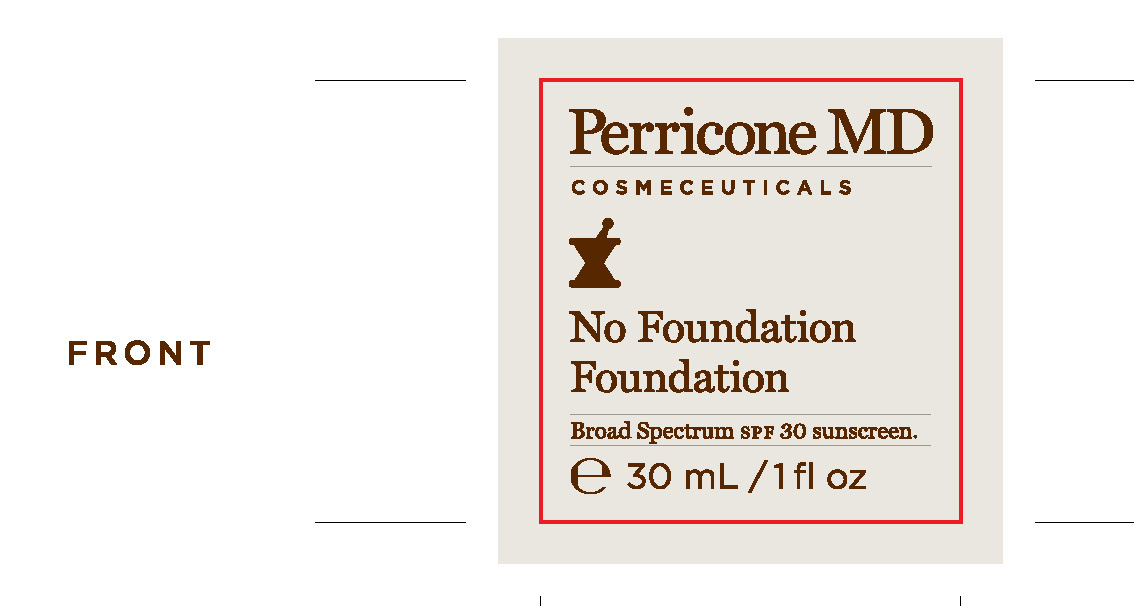 DRUG LABEL: Perricone
NDC: 45634-121 | Form: CREAM
Manufacturer: NV Perricone LLC
Category: otc | Type: HUMAN OTC DRUG LABEL
Date: 20120424

ACTIVE INGREDIENTS: ZINC OXIDE 12.2 mL/100 mL; TITANIUM DIOXIDE 3.2 mL/100 mL
INACTIVE INGREDIENTS: ALUMINUM HYDROXIDE; CHAMAEMELUM NOBILE FLOWER OIL; ARABIDOPSIS THALIANA; ASCORBIC ACID; ASCORBYL PALMITATE; BULNESIA SARMIENTOI WOOD OIL; BUTYLENE GLYCOL; ALKYL (C12-15) BENZOATE; C13-14 ISOPARAFFIN; MEDIUM-CHAIN TRIGLYCERIDES; CAPRYLYL GLYCOL; CEDRUS ATLANTICA BARK OIL; CERAMIDE 2; CETYL ALCOHOL; CITRIC ACID MONOHYDRATE; LEMON OIL; CORIANDER OIL; CYCLOMETHICONE 6; CYCLOMETHICONE 5; DIMETHICONE; DEANOL; GLYCYRRHIZINATE DIPOTASSIUM; EDETATE DISODIUM; ETHYLHEXYL PALMITATE; ETHYLHEXYLGLYCERIN; CLOVE OIL; GLYCERIN; GLYCERYL MONOSTEARATE; GLYCOLIC ACID; HEXYLENE GLYCOL; HYALURONIC ACID; ILEX PARAGUARIENSIS LEAF; FERRIC OXIDE RED; FERRIC OXIDE YELLOW; FERROSOFERRIC OXIDE; JASMINUM OFFICINALE FLOWER; LAURETH-7; EGG PHOSPHOLIPIDS; LIMONENE, (+/-)-; LINALOOL, (+/-)-; MICA; PALMITOYL OLIGOPEPTIDE; PEG-10 RAPESEED STEROL; PEG-100 STEARATE; POLYETHYLENE GLYCOL 400; PHENOXYETHANOL; DATE; POLYACRYLAMIDE (1500 MW); CLARY SAGE; CLARY SAGE OIL; SILICON DIOXIDE; SILICA DIMETHYL SILYLATE; SODIUM LACTATE; SORBITAN MONOSTEARATE; STEARIC ACID; TEPRENONE; TETRAHEXYLDECYL ASCORBATE; .ALPHA.-LIPOIC ACID; TOCOPHEROL; TRIBEHENIN; TRIETHOXYCAPRYLYLSILANE; WHEAT BRAN; VIOLA ODORATA FLOWERING TOP; WATER; XANTHAN GUM

No Foundation Foundation

Active Ingredient Purpose

Zinc Oxide 12.2% Sunscreen

Titanium Dioxide 3.2% Sunscreen

Uses

Helps Prevent sunburn

Keep out of reach of children

If swallowed get medical help or contact a Poison Control Center right away.

stop use and ask a doctor if

rash occurs

Warnings

For external use only

Do not use on damaged or broken skin

When using this product

Keep out of eyes. Rinse with water to remove

Directions

Dr. Perricone recommends applying evenly in gentle circular motions on top of treatment and or moisturizer. Can be re-applied as neccesary. Compatible with all Perricone MD products

Apply generously and evenly 15 minutes before sun exposure.

Use a water resistant sunscreen if swimming or sweating.

Reapply at least every 2 hours.

Not for use on children.

INACTIVE INGREDIENT

Aluminum Hydroxide, Anthemis Nobilis Flower Oil, Arabidopsis Thaliana Extract, Ascorbic Acid, Ascorbyl Palmitate, Bulnesia Sarmientoi Wood Oil, Butlylene Glycol, C12-15 Alkyl Benzoate, C13-14 Isoparaffin, Caprylic/Capric Triglyceride, Caprylyl Glycol, Cedrus Atlantica Bark Oil, Ceramide 2, Cetyl Alcohol, Citric Acid, Citrus Medica Limonium (Lemon) Peel Oil, Coriandrum Sativum (Coriander) Fruit Oil, Cyclohexasiloxane, Cyclopentasiloxane, Dimethicone, Dimethyl MEA, Dipotassium Glycyrrhizate, Disodium EDTA, Ethylhexyl Palmitate, Ethylhexylglycerin, Eugenia Caryophyllus (Clove) Flower Oil, Fragrance, Glycerin, Glyceryl Stearate, Glycolic acid, Hexylene Glycol, Hyaluronic Acid, Ilex Paraguariensis Leaf Extract, Iron Oxides (CI 77491, CI 77492, CI 77499). Jasminum Officinale (Jasmine) Oil, Laureth-7, Lecithin, Limonene, Linalool, Mica, Microccocus Lysate, Palmitoyl Oligopeptide, PEG-10 Rapeseed oil, PEG-100 Stearate, PEG-8, Phenoxyethanol, Phoenix Dactylifera (Date) Fruit Extract, Plankton Extract, Polyacrylamide, Polyglyceryl-3 Polydimethylsiloxyethyl Dimethicone, Salvia Sclarea (Clary) Extract, Salvia Sclarea (Clary) Oil, Silica, Dimethyl Silylate, Sodium Lactate, Sorbitan Stearate, Stearic Acid, Teprenone, Tetrahexyldecyl Ascorbate, Thioctic Acid, Tocopheryl Linoleate/Oleate, Tribehenin, Triethoxycaprylylsilane, Triethoxysilyethyl Polymethylsiloxyethyl Hexyl Dimethicone, Triticum Vulgare (Wheat) Bran Extract, Viola Odorata Flower/Leaf Extract, Water, Xanthan Gum

PACKAGE LABEL

Perricone MD Cosmeceuticals

No Foundation Foundation

Broad Spectrum SPF 30 sunscreen

30 mL/1 fl oz